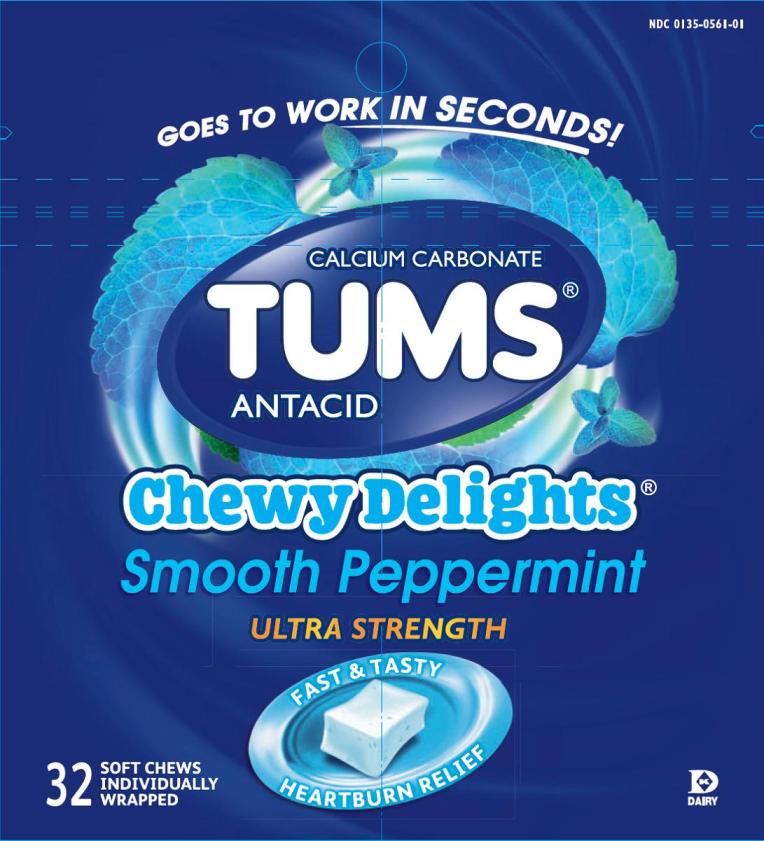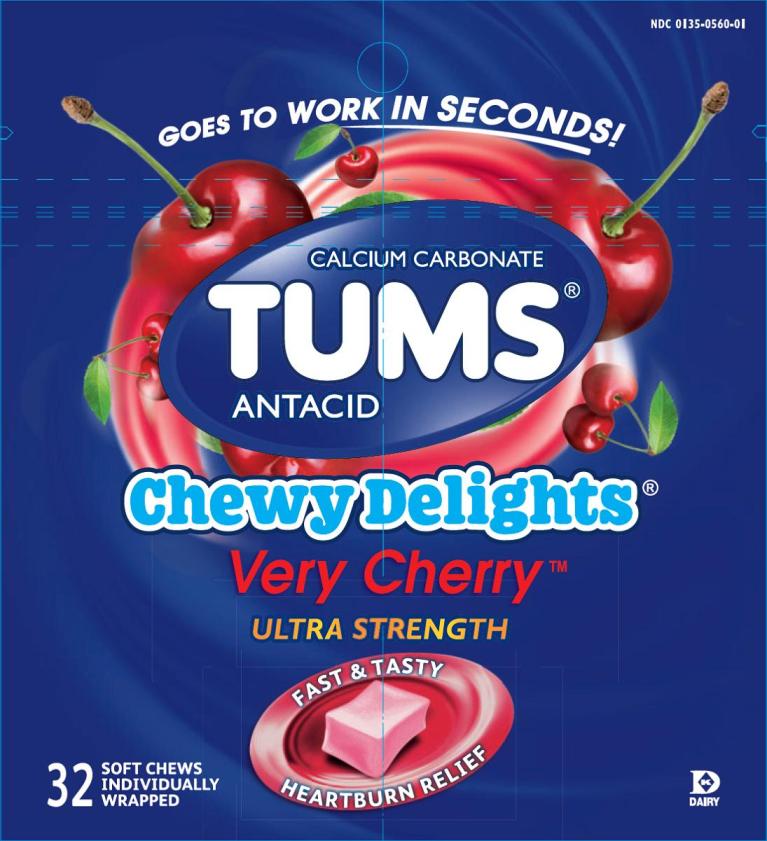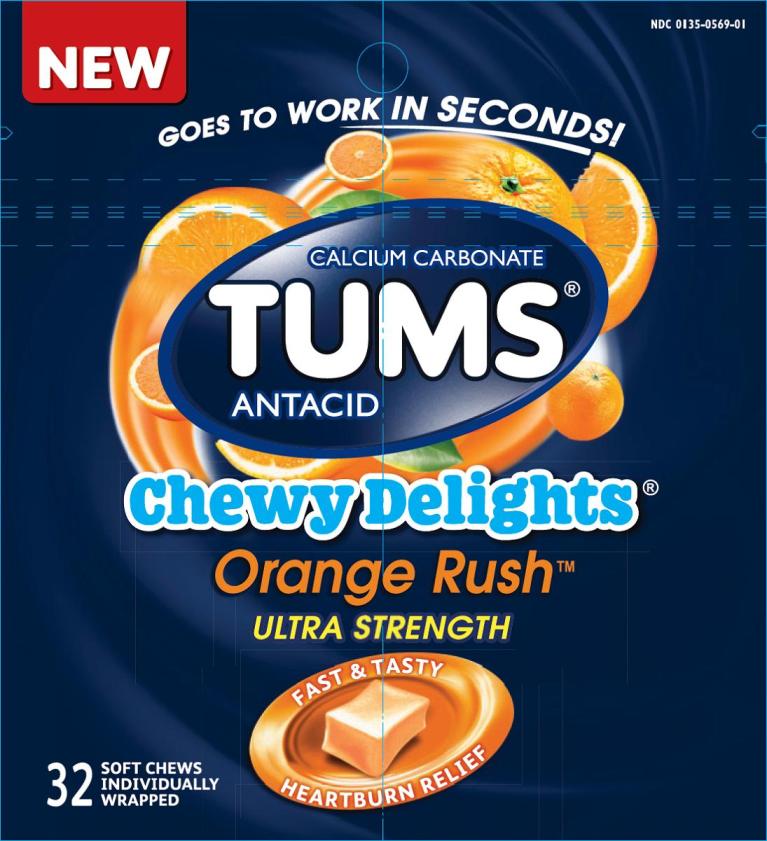 DRUG LABEL: Tums

NDC: 0135-0561 | Form: BAR, CHEWABLE
Manufacturer: Haleon US Holdings LLC
Category: otc | Type: HUMAN OTC DRUG LABEL
Date: 20240302

ACTIVE INGREDIENTS: CALCIUM CARBONATE 1177 mg/1 1
INACTIVE INGREDIENTS: STARCH, CORN; CORN SYRUP; FD&C BLUE NO. 1; GLYCERIN; ACACIA; HYDROGENATED COCONUT OIL; COW MILK; POTASSIUM SORBATE; PROPYLENE GLYCOL; LECITHIN, SOYBEAN; SUCROSE

Drug Facts

Active ingredient (in each chew)

Calcium carbonate USP 1177 mg

Purpose

Antacid

Uses

Relieves:

- heartburn
- sour stomach
- acid indigestion
- upset stomach associated with these symptoms

Warnings

Ask a doctor or pharmacist before use if you are

presently taking a prescription drug. Antacids may interact with certain prescription drugs.

When using this product

- do not take more than 6 chews in 24 hours
- if pregnant, do not take more than 4 chews in 24 hours
- do not use the maximum dosage for more than 2 weeks except under the advice and supervision of a doctor

Directions

- adults and children 12 years of age and over:chew and swallow 2-3 chews as symptoms occur, or as directed by a doctor
- do not take for symptoms that persist for more than 2 weeks unless advised by a doctor

Other information

- each chew contains:elemental calcium 470 mg, magnesium 5 mg
- do not store above 25°C (77°F)

Inactive ingredients (Smooth Peppermint)

corn starch, corn syrup, corn syrup solids, FD&C blue #1, flavors, glycerin, gum arabic, hydrogenated coconut oil, non-fat dairy milk, potassium sorbate, propylene glycol, soy lecithin, sucrose

Inactive ingredients (Very Cherry)

corn starch, corn syrup, corn syrup solids, FD&C red #40 lake, flavors, glycerin, hydrogenated coconut oil, non-fat dairy milk, propylene glycol, soy lecithin, sucrose

Inactive ingredients (Orange Rush)

corn starch, corn syrup, corn syrup solids, FD&C yellow #6 lake, flavors, glycerin, hydrogenated coconut oil, modified food starch, non-fat dairy milk, propylene glycol, soy lecithin, sucrose

Questions or Comments?

1-800-897-7535 weekdays

Principal Display Panel

NDC 0135-0561-01

TUMS®

CALCIUM CARBONATE

ANTACID

Chewy Delights®

Smooth Peppermint

ULTRA STRENGTH

GOES TO WORK IN SECONDS!

32SOFT CHEWS INDIVIDUALLY WRAPPED

FAST & TASTY

HEARTBURN RELIEF

DAIRY

Tamper Evident:Do not use if packaging is torn or damaged.

Distributed By:

GlaxoSmithKline

Consumer Healthcare, L.P.

Moon Township, PA 15108

TUMS and logo device are trademarks of the GSK group of companies.

©2014 GSK group of companies.

All Rights Reserved

103608XA

Principal Display Panel

NDC 0135-0560-01

TUMS®

CALCIUM CARBONATE

ANTACID

Chewy Delights®

Very Cherry™

ULTRA STRENGTH

GOES TO WORK IN SECONDS!

32SOFT CHEWS INDIVIDUALLY WRAPPED

FAST & TASTY

HEARTBURN RELIEF

DAIRY

Tamper Evident:Do not use if packaging is torn or damaged.

Distributed By:

GlaxoSmithKline

Consumer Healthcare, L.P.

Moon Township, PA 15108

TUMS and logo device are trademarks of the GSK group of companies.

©2014 GSK group of companies.

All Rights Reserved

103614XA

Principal Display Panel

NDC 0135-0569-01

TUMS®

CALCIUM CARBONATE

ANTACID

Chewy Delights®

Orange Rush™

ULTRA STRENGTH

GOES TO WORK IN SECONDS!

32SOFT CHEWS INDIVIDUALLY WRAPPED

FAST & TASTY

HEARTBURN RELIEF

Tamper Evident:Do not use if packaging is torn or damaged.

Distributed By:

GlaxoSmithKline

Consumer Healthcare, L.P.

Moon Township,

PA 15108

TUMS and logo device are trademarks of the GSK group of companies.

103438XA